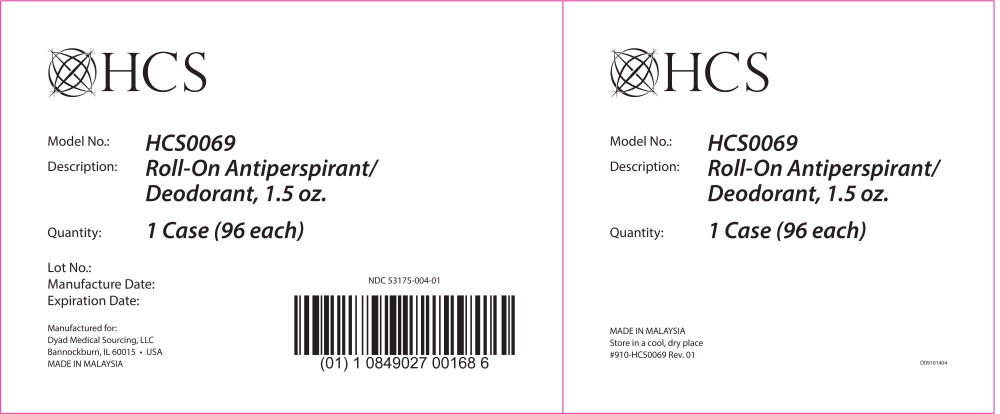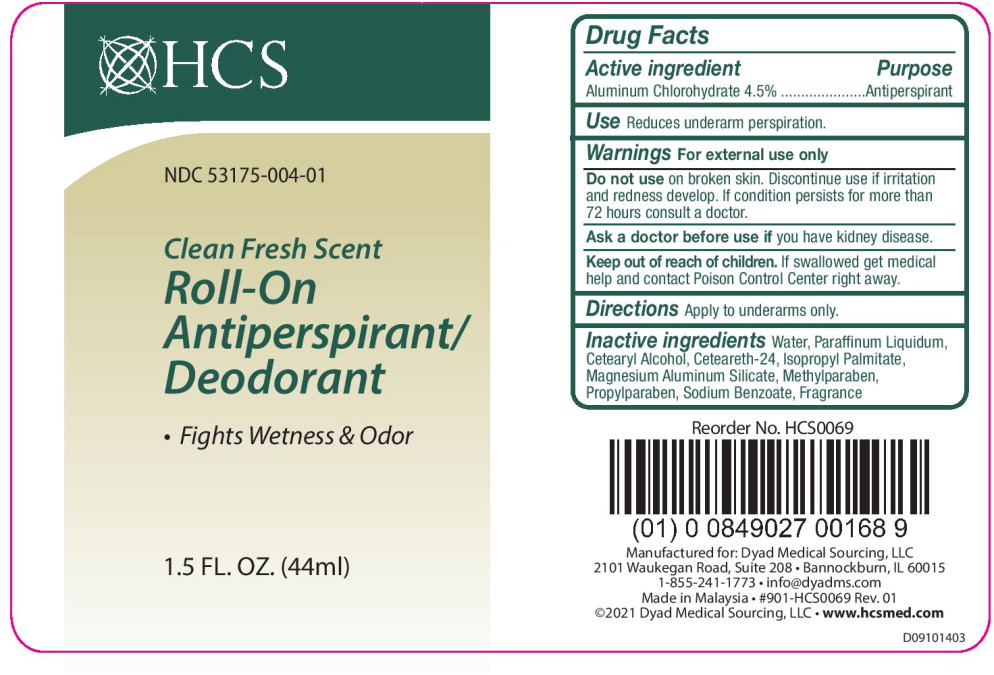 DRUG LABEL: HCS Roll-On Antiperspirant
NDC: 53175-004 | Form: LIQUID
Manufacturer: Dyad Medical Sourcing, LLC
Category: otc | Type: HUMAN OTC DRUG LABEL
Date: 20220413

ACTIVE INGREDIENTS: Aluminum Chlorohydrate 45 mg/1 mL
INACTIVE INGREDIENTS: Water; Mineral Oil; Cetostearyl Alcohol; Isopropyl Palmitate; Magnesium Aluminum Silicate; Methylparaben; Propylparaben; Sodium Benzoate

Drug Facts

Active Ingredient

Aluminum Chlorohydrate 4.5%

Purpose

Antiperspirant

Use

Reduces underarm perspiration.

Warnings

For external use only

Do not use on broken skin. Discontinue use if irritation and redness develop. If condition persists for more than 72 hours consult a doctor.

Ask a doctor before use if you have kidney disease.

Keep out of reach of children. If swallowed get medical help and contact Poison Control Center right away.

Directions

Apply to underarms only.

Inactive Ingredients

Water, Paraffinum Liquidum, Cetearyl Alcohol, Ceteareth-24, Isopropyl Palmitate, Magnesium Aluminum Silicate, Methylparaben, Propylparaben, Sodium Benzoate, Fragrance

Principal Display Panel – 96 each

HCS

Model No.: HCS0069

Description: Roll-On Antiperspirant/

Deodorant, 1.5 oz.

Quantity: 1 Case (96 each)

Lot No.:

Manufacture Date:

Expiration Date:

Manufactured for:

Dyad Medical Sourcing, LLC

Bannockburn, IL 60015 • USA

MADE IN MALAYSIA

NDC 53175-004-01

Principal Display Panel – 1 Bottle

HCS

NDC 53175-004-01

Clean Fresh Scent
Roll-On
Antiperspirant/
Deodorant

- Fights Wetness & Odor

1.5 FL. OZ. (44ml)